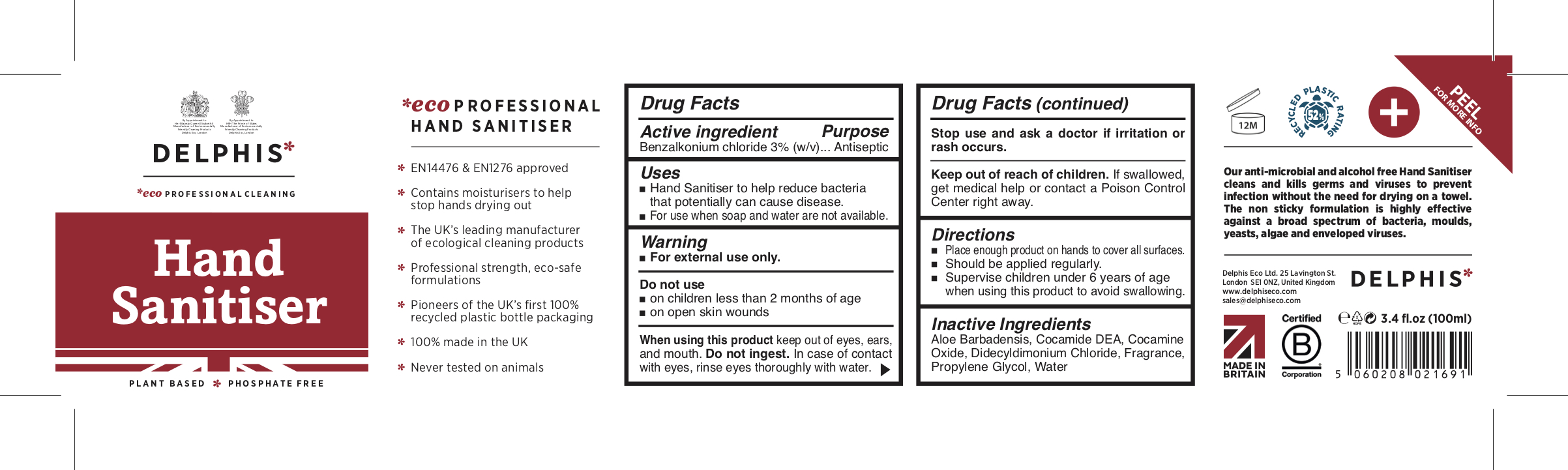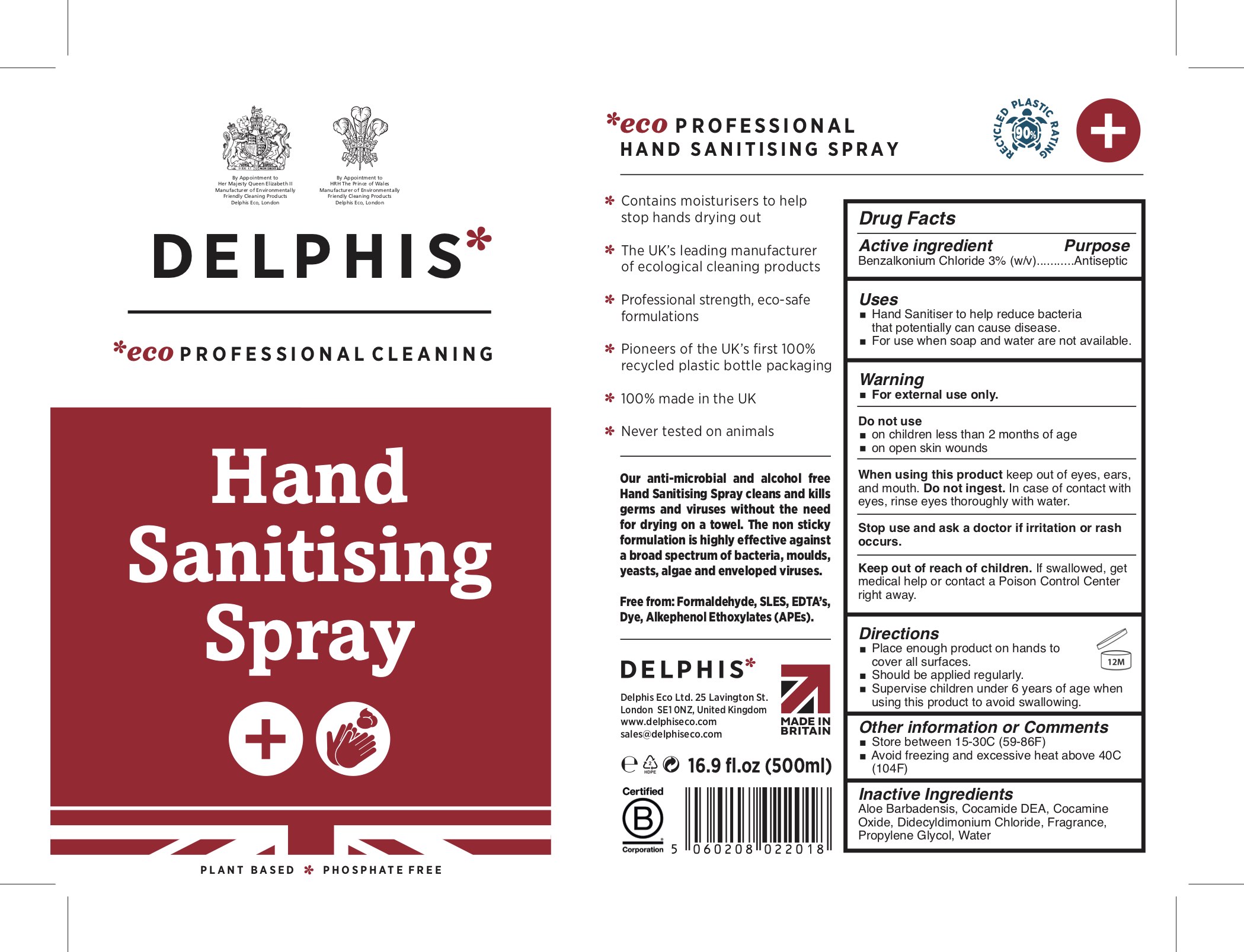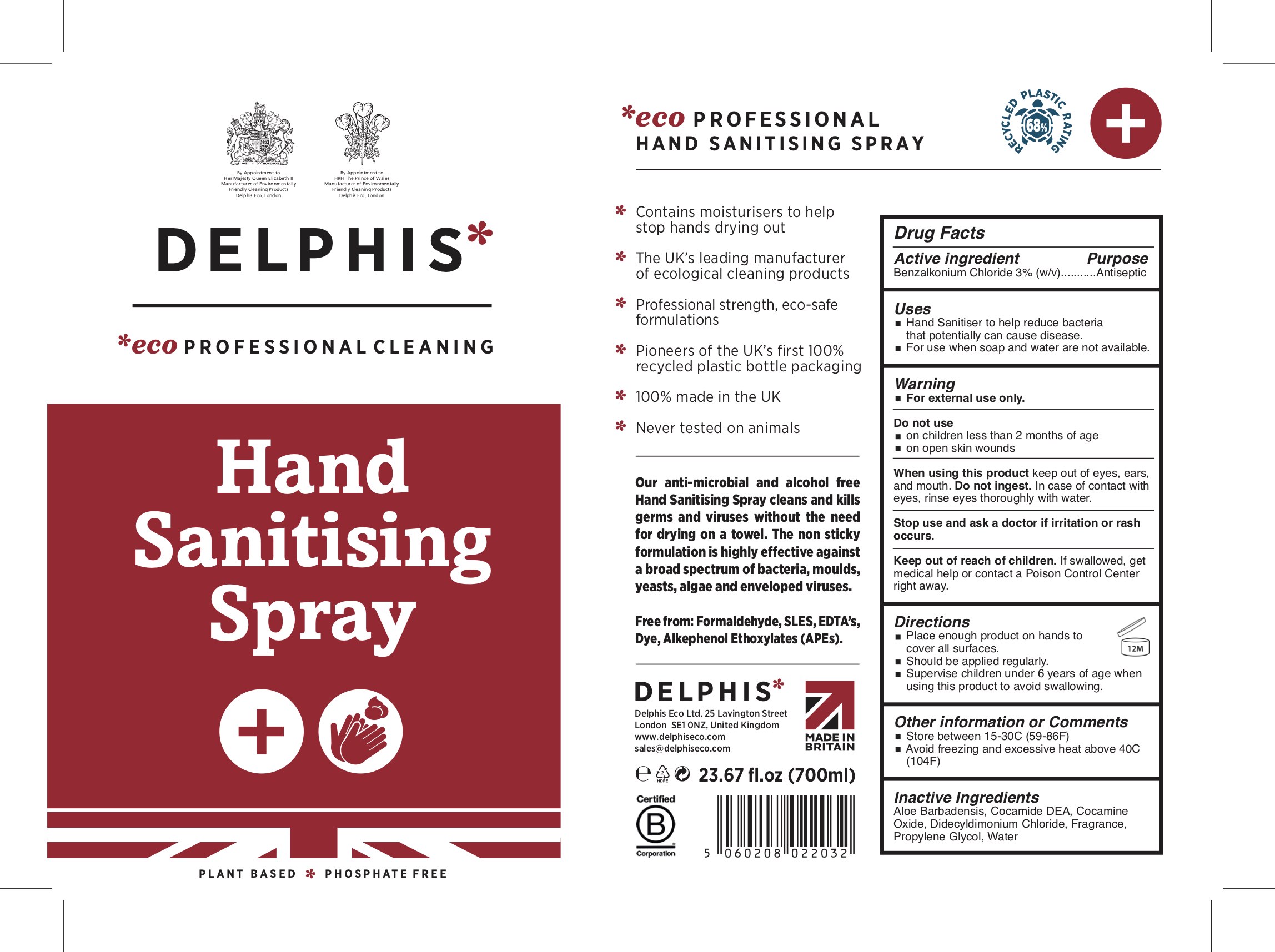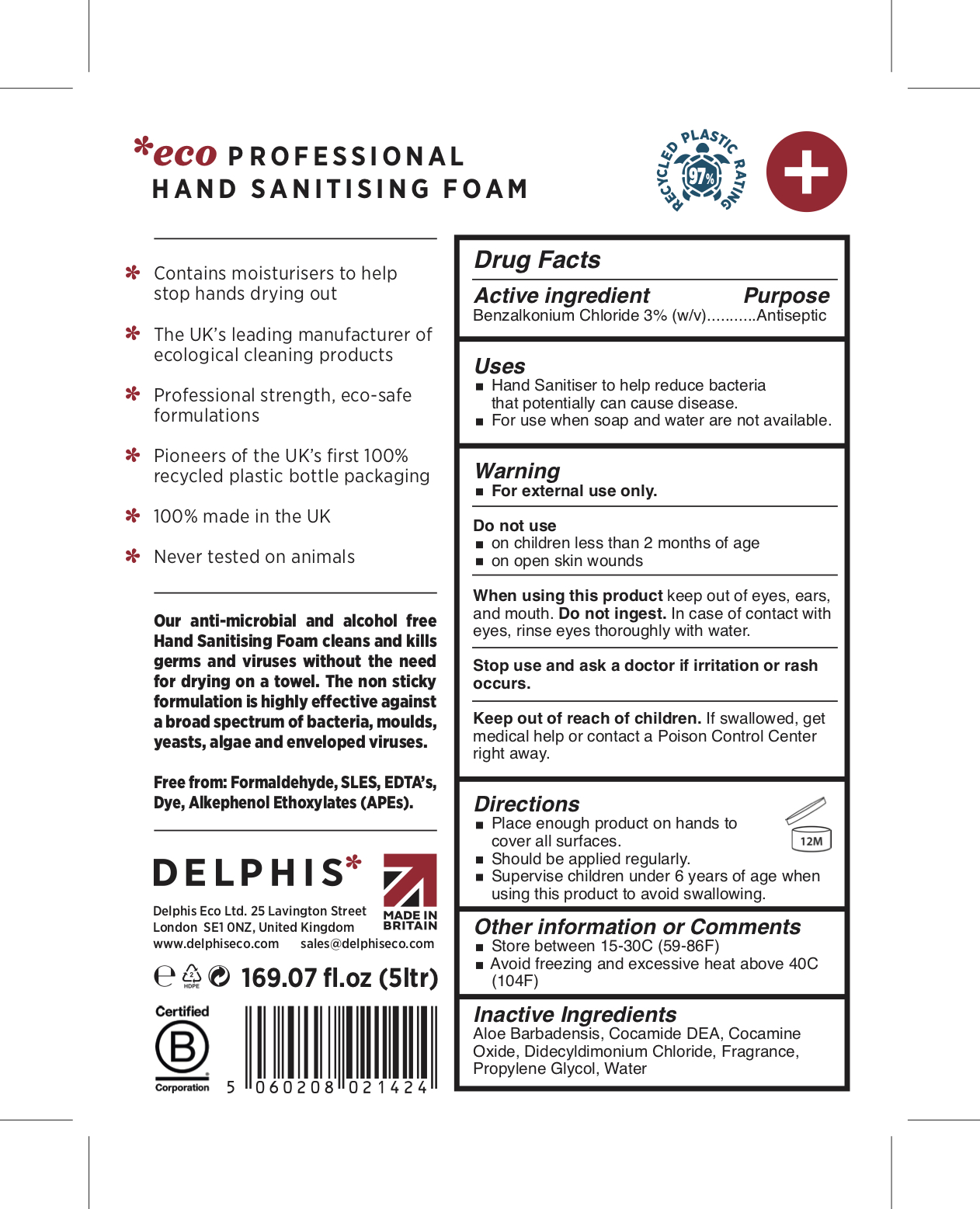 DRUG LABEL: Delphis Eco
NDC: 81560-003 | Form: LIQUID
Manufacturer: DELPHIS ECO LIMITED
Category: otc | Type: HUMAN OTC DRUG LABEL
Date: 20210225

ACTIVE INGREDIENTS: BENZALKONIUM CHLORIDE 3 g/100 mL
INACTIVE INGREDIENTS: WATER; ALOE VERA LEAF; DIDECYLDIMONIUM CHLORIDE; PROPYLENE GLYCOL; COCAMINE OXIDE; COCO DIETHANOLAMIDE

Delphis Eco Hand Sanitiser

Active Ingredient

Benzalkonium Chloride 3.0% (w/v)

Purpose

Antiseptic

Uses

- Hand sanitiser to help reduce bacteria that potentially can cause disease.
- For use when soap and water are not available.

Warning

- For external use only.

Do not use

- on children less than 2 months of age
- on open skin wounds

When using this product keep out of eyes, ears, and mouth. Do not ingest. In case of contact with eyes, rinse eyes thoroughly with water.

Stop use and ask a doctor if irritation or rash occurs.

Keep out of reach of children. If swallowed, get medical help or contact a Poison Control Center right away.

Directions

- Place enough product on hands to cover all surfaces.
- Should be applied regularly.
- Supervise children under 6 years of age when using this product to avoid swallowing.

Other Information or Comments

- Store between 15-30C (59-86F)
- Avoid freezing and excessive heat above 40C (104F)

Inactive Ingredients

Aloe Barbadensis, Cocamide DEA, Cocamine Oxide, Didecyldimonium chloride, Fragrance, Propylene glycol, Water

Principal Display Panel

Delphis Eco Hand Sanitiser (100 mL) NDC: 81560-001-01

Delphis Eco Hand Sanitising Spray (500 mL) NDC: 81560-002-05

Delphis Eco Hand Sanitising Spray (700 mL) NDC: 81560-002-07

Delphis Eco Hand Sanitising Foam (5 L) NDC: 81560-003-50